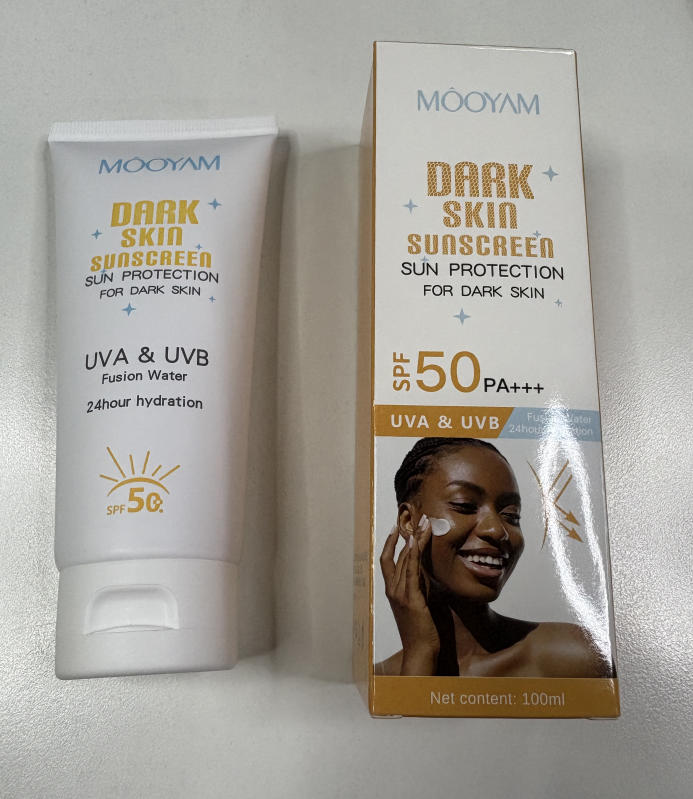 DRUG LABEL: MOOYAM Dark Skin Sunscreen
NDC: 84753-038 | Form: CREAM
Manufacturer: Guangdong Bisutang Biotechnology Co., LTD
Category: otc | Type: HUMAN OTC DRUG LABEL
Date: 20251029

ACTIVE INGREDIENTS: ETHYLHEXYL METHOXYCINNAMATE 9.993 g/100 mL; TITANIUM DIOXIDE 7.8 g/100 mL
INACTIVE INGREDIENTS: CARAMEL; CENTELLA ASIATICA; STEARIC ACID; BUTYLENE GLYCOL; CI 19140; ALUMINUM HEXAFLUOROSILICATE NONAHYDRATE; C13-14 ISOPARAFFIN; GLYCERIN; POLYACRYLAMIDE (10000 MW); SORBITAN SESQUIOLEATE; CAMELLIA SINENSIS LEAF; PROPYLENE GLYCOL; PEG-100 STEARATE; FRAGRANCE GREEN FLORAL ORC2000883; ALUMINA; POLYGONUM CUSPIDATUM ROOT; BHT; GLYCYRRHIZA GLABRA (LICORICE) ROOT; CI 16035; ROSMARINUS OFFICINALIS (ROSEMARY) LEAF OIL; ETHYLHEXYL PALMITATE; LAURETH-7; METHYLPARABEN; SODIUM CHLORIDE; WATER; PHENOXYETHANOL; MATRICARIA CHAMOMILLA; AKA102; GLYCERYL STEARATE; CI 15985; SCUTELLARIA BAICALENSIS ROOT

Uses

Helps prevent sunburn If used as directed with other sun protection measures (see Directions), decreases the risk of skin cancer and early aging caused by the sun.

Directions
• Apply generously and evenly to face and neck 15-20 minutes before sun exposure.
• Reapply at least every 2 hours
• Use a water-resistant sunscreen when swimming or sweating.

• Sun Protection Measures. Spending time in the sun increases your risk of skin cancer and early aging.
To reduce this risk, regularly use a sunscreen with a Broad Spectrum SPF value of 15 or higher and other sun protection measures including:
- Limiting time in the sun, especially from 10 a.m. - 2 p.m.
- Wear long-sleeved shirts, pants, hats, and sunglasses.
• Children under 6 months: Ask a doctor.

ACTIVE INGREDIENT

ETHYLHEXYL METHOXYCINNAMATE ---9.993
TITANIUM DIOXIDE ----7.8

KEEP OUT OF REACH OF CHILDREN

PURPOSE

Sunscreen

Warnings

Do not use on damaged or broken skin.

For external use only.

When using this product keep out of eyes.

If product gets into the eyes, rinse with water to remove

Stop use and consult a doctor if rash occurs.

INACTIVE INGREDIENT

WATER
PROPYLENE GLYCOL
STEARIC ACID
ETHYLHEXYL PALMITATE
GLYCERIN
GLYCERYL STEARATE
PEG-100 STEARATE
PHENOXYETHANOL
CARAMEL
POLYACRYLAMIDE
C13-14 ISOPARAFFIN
SORBITAN SESQUIOLEATE
METHYLPARABEN
LAURETH-7
FRAGRANCE
BUTYLENE GLYCOL
CI 19140
AKA102
L5630XRC87
SODIUM CHLORIDE
ALUMINA
CENTELLA ASIATICA EXTRACT
POLYGONUM CUSPIDATUM ROOT EXTRACT
SCUTELLARIA BAICALENSIS ROOT EXTRACT
BHT
CAMELLIA SINENSIS LEAF EXTRACT
GLYCYRRHIZA GLABRA (LICORICE) ROOT EXTRACT
CHAMOMILLA RECUTITA (MATRICARIA) FLOWER EXTRACT
ROSMARINUS OFFICINALIS (ROSEMARY) LEAF EXTRACT
CI 16035
CI 15985